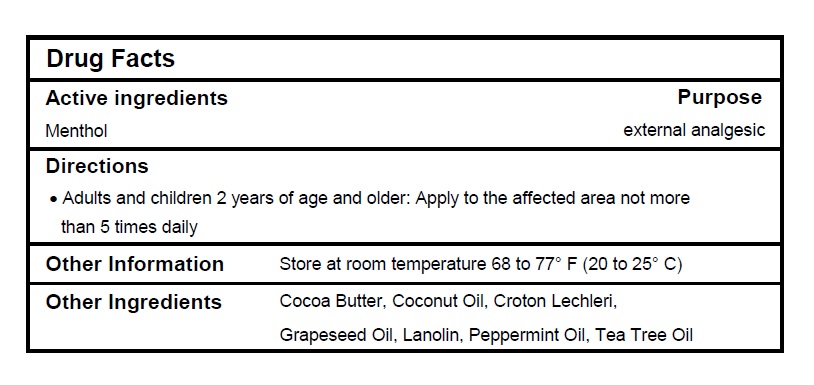 DRUG LABEL: COLDSORE BOMB
NDC: 72883-020 | Form: OINTMENT
Manufacturer: Envisionate PSJ LLC
Category: otc | Type: HUMAN OTC DRUG LABEL
Date: 20201002

ACTIVE INGREDIENTS: MENTHOL 1 g/100 g
INACTIVE INGREDIENTS: LANOLIN; COCOA BUTTER; COCONUT OIL; GRAPE SEED OIL; PEPPERMINT OIL; CROTON LECHLERI RESIN; TEA TREE OIL

Drug Facts

Active ingredients

Menthol 1%

Purpose

External analgesic

Directions

- Adults and children 2 years of age and older: Apply to the affected area not more than 5 times daily.

Other Information

Store at room temperature 68 to 77°F (20 to 25ºC).

Inactive Ingredients

Cocoa Butter, Coconut Oil, Croton Lechleri, Grapeseed Oil, Lanolin, Peppermint Oil, Tea Tree Oil